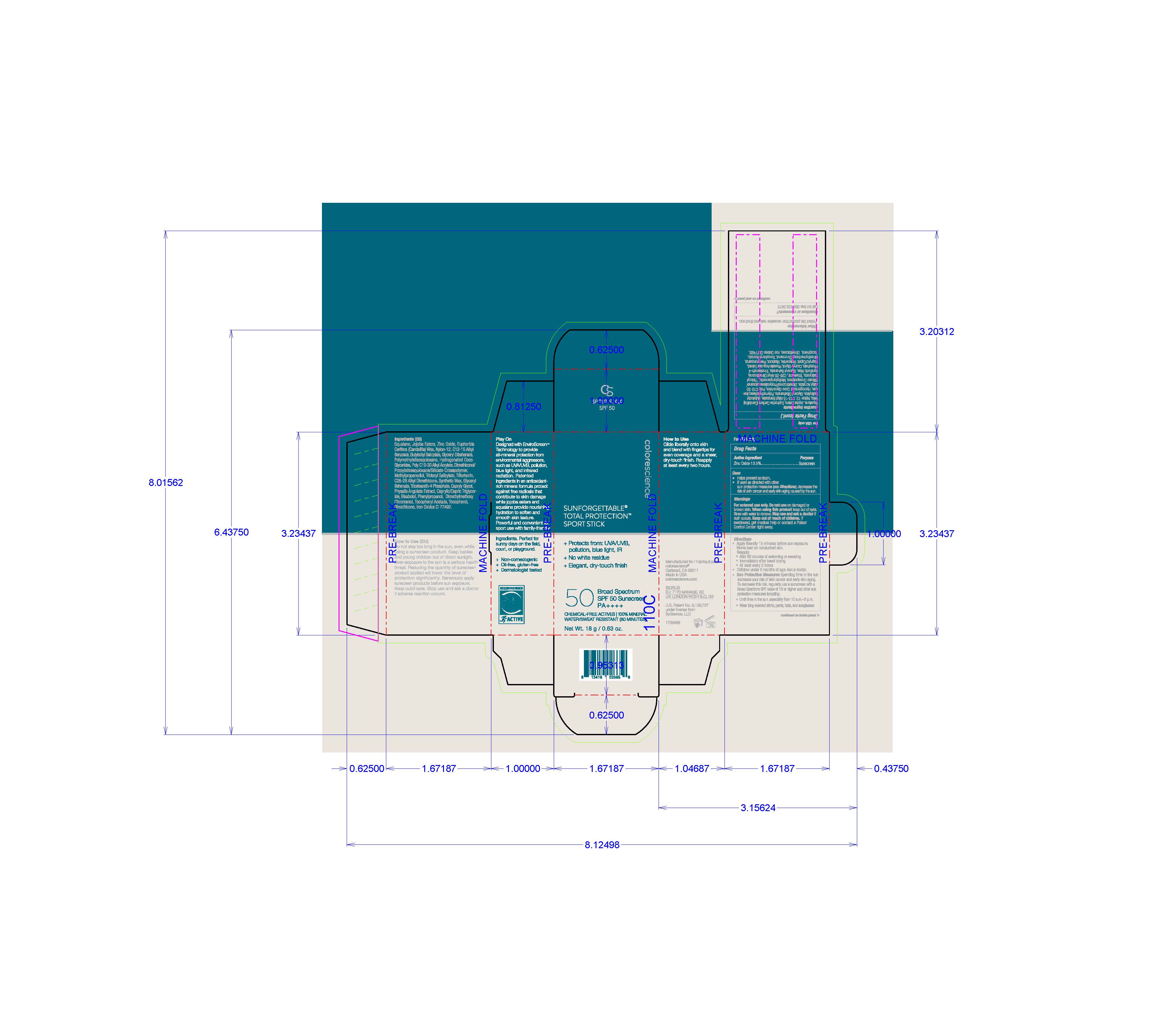 DRUG LABEL: Sunforgettable Total Protection Sport Stick
NDC: 68078-050 | Form: STICK
Manufacturer: Colorescience
Category: otc | Type: HUMAN OTC DRUG LABEL
Date: 20251015

ACTIVE INGREDIENTS: ZINC OXIDE 135 mg/1 g
INACTIVE INGREDIENTS: PHYSALIS ANGULATA; .ALPHA.-BISABOLOL, (+)-; FERRIC OXIDE YELLOW; TOCOPHEROL; DIMETHICONE; DIMETHICONOL/PROPYLSILSESQUIOXANE/SILICATE CROSSPOLYMER (450000000 MW); DIMETHYLMETHOXY CHROMANOL; TRIDECYL SALICYLATE; SQUALANE; CAPRYLYL GLYCOL; HYDROGENATED COCO-GLYCERIDES; SYNTHETIC WAX (2900 MW); BUTYLOCTYL SALICYLATE; TRIBEHENIN; METHYLPROPANEDIOL; NYLON-12; POLYMETHYLSILSESQUIOXANE (11 MICRONS); GLYCERYL DIBEHENATE; PHENYLPROPANOL; TRICETEARETH-4 PHOSPHATE; CANDELILLA WAX; ALKYL (C12-15) BENZOATE

Sunforgettable Total Protection Sport Stick